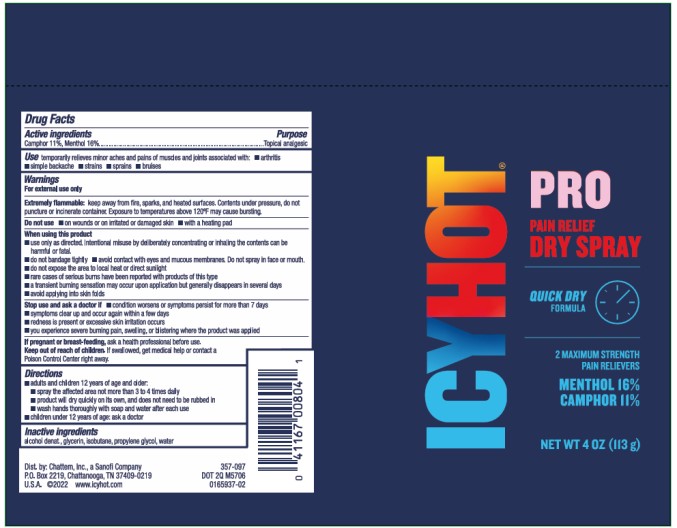 DRUG LABEL: Icy Hot Pro Dry
NDC: 41167-0080 | Form: SPRAY
Manufacturer: Chattem, Inc.
Category: otc | Type: HUMAN OTC DRUG LABEL
Date: 20230301

ACTIVE INGREDIENTS: MENTHOL 16 g/100 mL; CAMPHOR (SYNTHETIC) 11 g/100 mL
INACTIVE INGREDIENTS: ALCOHOL; GLYCERIN; ISOBUTANE; PROPYLENE GLYCOL; WATER

Icy Hot Pro Dry Spray

ICY HOT PRO DRY SPRAY

Drug Facts

Purpose

Camphor 11%, Menthol 16%.............................................................................................................Topical analgesic

Use

temporarily relieves minor aches and pains of muscles and joints associated with:

■ arthritis ■ simple backache ■ strains ■ sprains ■ bruises

Warnings

For external use only

Extremely flammable: keep away from fire, sparks, and heated surfaces. Contents under pressure, do not puncture or incinerate container. Exposure to temperatures above 120°F may cause bursting.

Do not use

■ on wounds or on irritated or damaged skin

■ with a heating pad

When using this product

■ use only as directed. Intentional misuse by deliberately concentrating or inhaling the contents can be harmful or fatal.

■ do not bandage tightly

■ avoid contact with eyes and mucous membranes. Do not spray in face or mouth.

■ do not expose the area to local heat or direct sunlight

■ rare cases of serious burns have been reported with products of this type

■ a transient burning sensation may occur upon application but generally disappears in several days

■ avoid applying into skin folds

Stop use and ask a doctor if

■ condition worsens or symptoms persist for more than 7 days

■ symptoms clear up and occur again within a few days

■ redness is present or excessive skin irritation occurs

■ you experience severe burning pain, swelling, or blistering where the product was applied

Keep out of reach of children.

If swallowed, get medical help or contact a Poison Control Center right away.

Directions

- adults and children 12 years of age and older:
  ▪ spray the affected area not more than 3 to 4 times daily
  ▪ product will dry quickly on its own, and does not need to be rubbed in
  ▪ wash hands thoroughly with soap and water after each use
- children under 12 years of age: ask a doctor

Inactive ingredients:

alcohol denat., glycerin, isobutane, propylene glycol, water

PRINCIPAL DISPLAY PANEL

ICY HOT
PRO
Pain Relief
DRY SPRAY
NET WT 4 oz (113g)